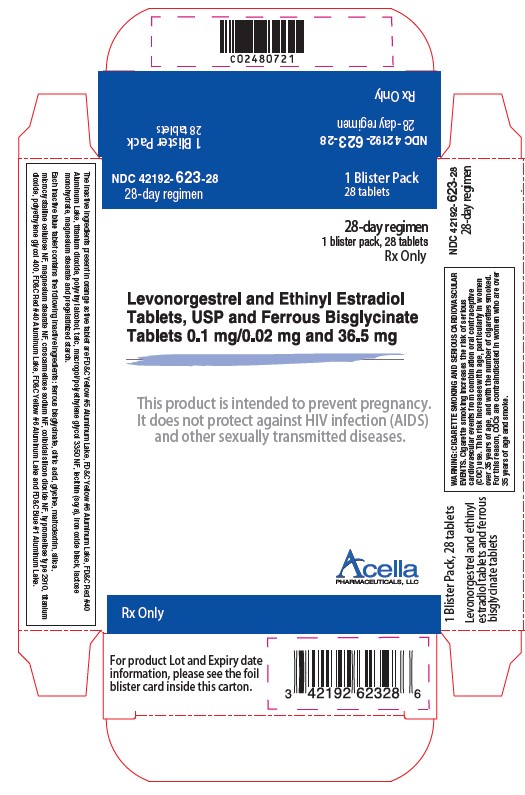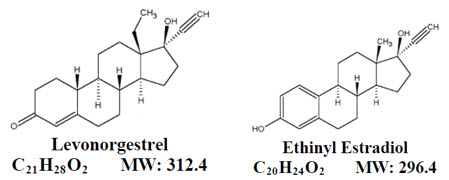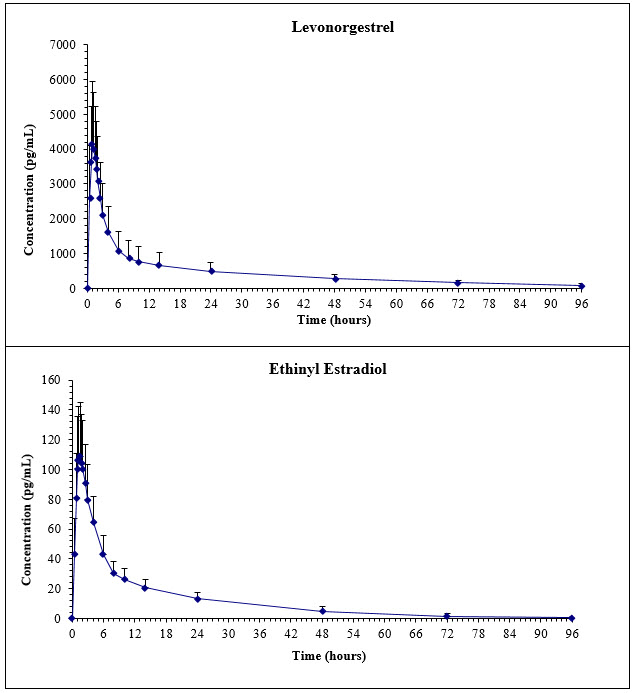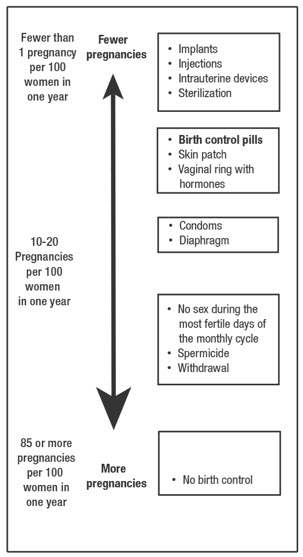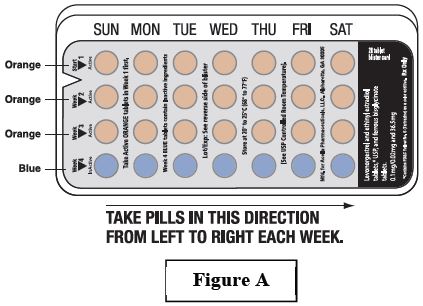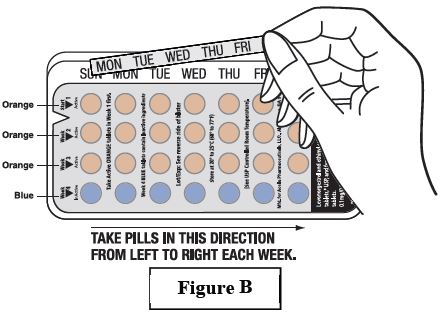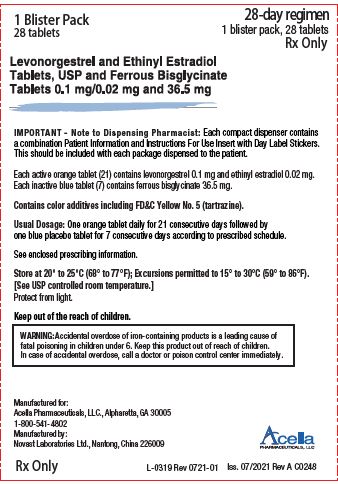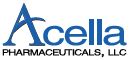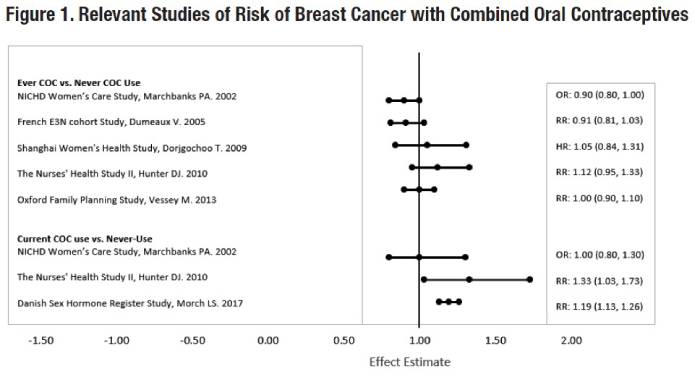 DRUG LABEL: levonorgestrel and ethinyl estradiol
NDC: 42192-623 | Form: KIT | Route: ORAL
Manufacturer: Acella Pharmaceuticals
Category: prescription | Type: HUMAN PRESCRIPTION DRUG LABEL
Date: 20251205

ACTIVE INGREDIENTS: LEVONORGESTREL 0.1 mg/1 1; ETHINYL ESTRADIOL 0.02 mg/1 1
INACTIVE INGREDIENTS: FD&C YELLOW NO. 5; FD&C YELLOW NO. 6; FD&C RED NO. 40; TITANIUM DIOXIDE; POLYVINYL ALCOHOL, UNSPECIFIED; TALC; POLYETHYLENE GLYCOL 3350; LECITHIN, SOYBEAN; FERROSOFERRIC OXIDE; LACTOSE MONOHYDRATE; MAGNESIUM STEARATE; STARCH, CORN; FERROUS BISGLYCINATE; CITRIC ACID MONOHYDRATE; GLYCINE; MALTODEXTRIN; SILICON DIOXIDE; MICROCRYSTALLINE CELLULOSE; MAGNESIUM STEARATE; CROSCARMELLOSE SODIUM; HYPROMELLOSE, UNSPECIFIED; TITANIUM DIOXIDE; POLYETHYLENE GLYCOL 400; FD&C RED NO. 40; FD&C YELLOW NO. 6; FD&C BLUE NO. 1

HIGHLIGHTS OF PRESCRIBING INFORMATION

These highlights do not include all the information needed to use LEVONORGESTREL AND ETHINYL ESTRADIOL TABLETS AND FERROUS BISGLYCINATE TABLETS safely and effectively. See Full Prescribing Information for LEVONORGESTREL AND ETHINYL ESTRADIOL TABLETS AND FERROUS BISGLYCINATE TABLETS.
LEVONORGESTREL and ETHINYL ESTRADIOL tablets and FERROUS BISGLYCINATE tablets for oral administration
Initial U.S. Approval: 1997

WARNING: CIGARETTE SMOKING AND SERIOUS CARDIOVASCULAR EVENTS

See full prescribing information for complete boxed warning.

- Levonorgestrel and ethinyl estradiol tablets and ferrous bisglycinate tablets are contraindicated in women over 35 years old who smoke. (4)
- Cigarette smoking increases the risk of serious cardiovascular events from combination oral contraceptives (COC) use. (4)

1 INDICATIONS AND USAGE

Levonorgestrel and ethinyl estradiol tablets, USP and ferrous bisglycinate tablets are progestin/estrogen COC indicated for use by females of reproductive potential to prevent pregnancy. (1)

RECENT MAJOR CHANGES

Warnings and Precautions (5.11) 04/2022

2 DOSAGE AND ADMINISTRATION

- Take one tablet by mouth at the same time every day. (2.1)
- Take tablets in the order directed on the blister pack. (2.1)

3 DOSAGE FORMS AND STRENGTHS

Levonorgestrel and ethinyl estradiol tablets, USP and ferrous bisglycinate tablets consist of 28 tablets in the following order (3):

- 21 orange tablets (active), each containing 0.1 mg levonorgestrel and 0.02 mg ethinyl estradiol.
- 7 blue tablets (inactive placebo) each containing ferrous bisglycinate 36.5 mg. The ferrous bisglycinate tablets do not serve any therapeutic purpose. (3)

4 CONTRAINDICATIONS

- A high risk of arterial or venous thrombotic diseases (4)
- Liver tumors or liver disease (4)
- Undiagnosed abnormal uterine bleeding (4)
- Pregnancy (4)
- Breast cancer (4)
- Hypersensitivity of any of the components (4)
- Co-administration with Hepatitis C drug combinations containing ombitasvir/paritaprevir/ritonavir, with or without dasabuvir (4)

5 WARNINGS AND PRECAUTIONS

- Thrombotic Disorders and Other Vascular Problems: Stop levonorgestrel and ethinyl estradiol tablets and ferrous bisglycinate tablets if a thrombotic event occurs. Stop at least 4 weeks before through 2 weeks after major surgery. Start no earlier than 4 weeks after delivery, in women who are not breastfeeding. (5.1)
- Liver disease: Discontinue levonorgestrel and ethinyl estradiol tablets and ferrous bisglycinate tablets if jaundice occurs.(5.2)
- High blood pressure:If used in women with well-controlled hypertension, monitor blood pressure and stop levonorgestrel and ethinyl estradiol tablets and ferrous bisglycinate tablets if blood pressure rises significantly. (5.4)
- Carbohydrate and lipid metabolic effects:Monitor prediabetic and diabetic women taking levonorgestrel and ethinyl estradiol tablets and ferrous bisglycinate tablets. Consider an alternate contraceptive method for women with uncontrolled dyslipidemia. (5.6)
- Headache:Evaluate significant change in headaches and discontinue levonorgestrel and ethinyl estradiol tablets and ferrous bisglycinate tablets if indicated. (5.7)
- Bleeding Irregularities and Amenorrhea:Evaluate irregular bleeding or amenorrhea. (5.8)
- This product contains FD&C Yellow No. 5 (tartrazine) which may cause allergic-type reactions (including bronchial asthma) in certain susceptible persons. Although the overall incidence of FD&C Yellow No. 5 (tartrazine) sensitivity in the general population is low, it is frequently seen in patients who also have aspirin hypersensitivity (5.9)

6 ADVERSE REACTIONS

Common adverse reactions (≥2% of women): headache (14%), metrorrhagia (8%), dysmenorrhea and nausea (7% each), abdominal pain and breast pain (4% each), emotional lability and acne (3% each), and depression, amenorrhea, and vaginal moniliasis (2% each) (6.1)

To report SUSPECTED ADVERSE REACTIONS, contact Acella Pharmaceuticals, LLC at 1-800-541-4802 or FDA at 1-800-FDA-1088 or www.fda.gov/medwatch.

7 DRUG INTERACTIONS

Drugs or herbal products that induce certain enzymes, including CYP3A4, may decrease the effectiveness of COCs or increase breakthrough bleeding. Counsel patients to use a back-up method or alternative method of contraception when enzyme inducers are used with COCs.(7.1)

8 USE IN SPECIFIC POPULATIONS

- Nursing mothers: Advise use of another contraceptive method.
  Levonorgestrel and ethinyl estradiol tablets and ferrous bisglycinate tablets can decrease milk production. (8.2)

FULL PRESCRIBING INFORMATION

WARNING: CIGARETTE SMOKING AND SERIOUS CARDIOVASCULAR EVENTS

Cigarette smoking increases the risk of serious cardiovascular events from combination oral contraceptive (COC) use. This risk increases with age, particularly in women over 35 years of age, and with the number of cigarettes smoked. For this reason, COCs are contraindicated in women who are over 35 years of age and smoke [see Contraindications (4)] .

1 INDICATIONS AND USAGE

Levonorgestrel and ethinyl estradiol tablets, USP and ferrous bisglycinate tablets are indicated for use by females of reproductive potential to prevent pregnancy.

RECENT MAJOR CHANGES

Warnings and Precautions (5.11) 04/2022

2 DOSAGE AND ADMINISTRATION

2.1 How to Start Levonorgestrel and Ethinyl Estradiol Tablets, USP and Ferrous Bisglycinate Tablets

Levonorgestrel and ethinyl estradiol tablets, USP and ferrous bisglycinate tablets are dispensed in a blister card [see How Supplied/Storage and Handling (16)] . Levonorgestrel and ethinyl estradiol tablets, USP and ferrous bisglycinate tablets may be started using either a Day 1 start or a Sunday start (see Table 1). For the first cycle of a Sunday Start regimen, an additional method of contraception should be used until after the first 7 consecutive days of administration.

2.2 How to Take Levonorgestrel and Ethinyl Estradiol Tablets, USP and Ferrous Bisglycinate Tablets

Levonorgestrel and ethinyl estradiol tablets, USP and ferrous bisglycinate tablets (orange active tablets and blue placebo tablets) are swallowed whole once a day

Table 1: Instructions for Administration of Levonorgestrel and Ethinyl Estradiol Tablets, USP and Ferrous Bisglycinate Tablets
Starting COCs in women not currently using hormonal contraception (Day 1 Start or Sunday Start); Important:; Consider the possibility of ovulation and conception prior to initiation of this product.; Tablet Color:; - Levonorgestrel and ethinyl estradiol active tablets are orange (Day 1 to Day 21). - Ferrous bisglycinate placebo tablets are blue (Day 22 to Day 28). | Day 1 Start:; - Take first orange active tablet on the first day of menses. - Take subsequent orange active tablets once daily at the same time each day for a total of 21 days. - Take one blue placebo tablet daily for 7 days and at the same time of day that active tablets were taken. - Begin each subsequent pack on the same day of the week as the first cycle pack (i.e. on the day after taking the last inactive tablet).; Sunday Start:; - Take first active tablet on the first Sunday after the onset of menses. Due to the potential risk of becoming pregnant, use additional non-hormonal contraception (such as condoms or spermicide) for the first seven days of the patient’s first cycle pack of levonorgestrel and ethinyl estradiol tablets, USP and ferrous bisglycinate tablets. - Take subsequent orange tablets once daily at the same time each day for a total of 21 days. - Take one blue placebo tablet daily for the following 7 days and at the same time of day that active tablets were taken. - Begin each subsequent pack on the same day of the week as the first cycle pack (i.e., on the Sunday after taking the last inactive tablet) and additional non-hormonal contraceptive is not needed.
Switching to levonorgestrel and ethinyl estradiol tablets, USP and ferrous bisglycinate tablets from another hormonal contraceptive | Start on the same day that a new pack of the previous hormonal contraceptive would have started.
Switching from another contraceptive method to levonorgestrel and ethinyl estradiol tablets, USP and ferrous bisglycinate tablets | Start levonorgestrel and ethinyl estradiol tablets, USP and ferrous bisglycinate tablets:
- Transdermal patch | - On the day when next application would have been scheduled
- Vaginal ring | - On the day when next insertion would have been scheduled
- Injection | - On the day when next injection would have been scheduled
- Intrauterine contraceptive | - On the day of removal - If the IUD is not removed on first day of the patient’s menstrual cycle, additional non-hormonal contraceptive (such as condoms or spermicide) is needed for the first seven days of the first cycle pack.
- Implant | - On the day of removal
Complete instructions to facilitate patient counseling on proper tablet usage are located in the FDA-Approved Patient Labeling.

Starting Levonorgestrel and Ethinyl Estradiol Tablets, USP and Ferrous Bisglycinate Tablets after Abortion or Miscarriage

First-trimester

- After a first-trimester abortion or miscarriage, levonorgestrel and ethinyl estradiol tablets, USP and ferrous bisglycinate tablets may be started immediately. An additional method of contraception is not needed if levonorgestrel and ethinyl estradiol tablets, USP and ferrous bisglycinate tablets are started within 5 days after termination of the pregnancy.
- If levonorgestrel and ethinyl estradiol tablets, USP and ferrous bisglycinate tablets are not started within 5 days after termination of the pregnancy, the patient should use additional non-hormonal contraception (such as condoms or spermicide) for the first seven days of her first cycle pack of levonorgestrel and ethinyl estradiol tablets, USP and ferrous bisglycinate tablets.

Second-trimester

- Do not start until 4 weeks after a second-trimester abortion or miscarriage, due to the increased risk of thromboembolic disease. Start levonorgestrel and ethinyl estradiol tablets, USP and ferrous bisglycinate tablets following the instructions in Table 1 for Day 1 or Sunday start, as desired. If using Sunday start, use additional non-hormonal contraception (such as condoms or spermicide) for the first seven days of the patient’s first cycle pack of levonorgestrel and ethinyl estradiol tablets, USP and ferrous bisglycinate tablets. [See Contraindications (4), Warnings and Precautions (5.1), and FDA-Approved Patient Labeling.]

Starting Levonorgestrel and Ethinyl Estradiol Tablets, USP and Ferrous Bisglycinate Tablets after Childbirth

- Do not start until 4 weeks after delivery, due to the increased risk of thromboembolic disease. Start contraceptive therapy with levonorgestrel and ethinyl estradiol tablets, USP and ferrous bisglycinate tablets following the instructions in Table 1 for women not currently using hormonal contraception.
- If the woman has not yet had a period postpartum, consider the possibility of ovulation and conception occurring prior to use of levonorgestrel and ethinyl estradiol tablets, USP and ferrous bisglycinate tablets.
  [See Contraindications (4), Warnings and Precautions (5.1), Use in Specific Populations (8.1and 8.2), and FDA-Approved Patient Labeling] .

2.3 Missed Tablets

Table 2: Instructions for Missed Levonorgestrel and Ethinyl Estradiol Tablets, USP and Ferrous Bisglycinate Tablets
- If one orange active tablet is missed in Weeks 1, 2, or 3 | Take the tablet as soon as possible. Continue taking one tablet a day until the pack is finished.
- If two orange active tablets are missed in Week 1 or Week 2 | Take the two missed tablets as soon as possible and the next two active tablets the next day. Continue taking one tablet a day until the pack is finished.; Additional non-hormonal contraception (such as condoms or spermicide) should be used as back-up if the patient has sex within 7 days after missing tablets.
- If two orange tablets are missed in Week 3 or three or more orange active tablets are missed in a row in Weeks 1, 2, or 3 | Day 1 start:Throw out the rest of pack and start a new pack that same day.; Sunday start:Continue taking one tablet a day until Sunday, then throw out the rest of the pack and start a new pack that same day.; Additional non-hormonal contraception (such as condoms or spermicide) should be used as back-up if the patient has sex within 7 days after missing tablets.

2.4 Advice in Case of Gastrointestinal Disturbances

In case of severe vomiting or diarrhea, absorption may not be complete and additional contraceptive measures should be taken. If vomiting or diarrhea occurs within 3 to 4 hours after taking an active tablet, handle this as a missed tablet [see FDA-Approved Patient Labeling] .

3 DOSAGE FORMS AND STRENGTHS

Levonorgestrel and ethinyl estradiol tablets, USP, and ferrous bisglycinate tablets are available in a 28-tablet compact blister card with:

- 21 orange, round biconvex tablets (active) debossed with “A3” on one side and each containing levonorgestrel 0.10 mg and ethinyl estradiol 0.02 mg
- 7 blue, round biconvex tablets (inactive placebo) debossed with “F1” on one side and each containing ferrous bisglycinate 36.5 mg

The ferrous bisglycinate tablets do not serve any therapeutic purpose.

4 CONTRAINDICATIONS

Levonorgestrel and ethinyl estradiol tablets, USP and ferrous bisglycinate tablets are contraindicated in females who are known to have or develop the following conditions:

- A high risk of arterial or venous thrombotic disease. Examples include women who are known to:
  - Smoke, if over age 35 [see Boxed Warning and Warnings and Precautions (5.1)] .
  - Have deep vein thrombosis or pulmonary embolism, now or in the past [see Warnings and Precautions (5.1)] .
  - Have inherited or acquired hypercoagulopathies [see Warnings and Precautions (5.1)] .
  - Have cerebrovascular disease [see Warnings and Precautions (5.1)] .
  - Have coronary artery disease [see Warnings and Precautions (5.1)] .
  - Have thrombogenic valvular or thrombogenic rhythm diseases of the heart (for example, subacute bacterial endocarditis with valvular disease, or atrial fibrillation) [see Warnings and Precautions (5.1)] .
  - Have uncontrolled hypertension [see Warnings and Precautions (5.4)] .
  - Have diabetes mellitus with vascular disease [see Warnings and Precautions (5.6)] .
  - Have headaches with focal neurological symptoms or have migraine headaches with aura [see Warnings and Precautions (5.7)] .
    - Women over age 35 with any migraine headaches [see Warnings and Precautions (5.7)] .
- Liver tumors, benign or malignant, or liver disease [see Warnings and Precautions (5.2)].
- Undiagnosed abnormal uterine bleeding [see Warnings and Precautions (5.8)] .
- Pregnancy, because there is no reason to use COCs during pregnancy [see Warnings and Precautions (5.10) and Use in Specific Populations (8.1)] .
- Current diagnosis of, or history of, breast cancer, which may be hormone-sensitive [see Warnings and Precautions (5.11)] .
- Hypersensitivity to any of the components.
- Use of Hepatitis C drug combinations containing ombitasvir/paritaprevir/ritonavir, with or without dasabuvir, due to the potential for ALT elevations [see Warnings and Precautions (5.3)].

5 WARNINGS AND PRECAUTIONS

5.1 Thrombotic Disorders and Other Vascular Problems

- Stop levonorgestrel and ethinyl estradiol tablets and ferrous bisglycinate tablets if an arterial thrombotic event or venous thromboembolic (VTE) event occurs.
- Stop levonorgestrel and ethinyl estradiol tablets and ferrous bisglycinate tablets if there is unexplained loss of vision, proptosis, diplopia, papilledema, or retinal vascular lesions. Evaluate for retinal vein thrombosis immediately.
- If feasible, stop levonorgestrel and ethinyl estradiol tablets and ferrous bisglycinate tablets at least 4 weeks before and through 2 weeks after major surgery or other surgeries known to have an elevated risk of VTE as well as during the following prolonged immobilization.
- Start levonorgestrel and ethinyl estradiol tablets and ferrous bisglycinate tablets no earlier than 4 weeks after delivery, in women who are not breastfeeding. The risk of postpartum VTE decreases after the third postpartum week, whereas the risk of ovulation increases after the third postpartum week.
- The use of COCs increases the risk of VTE. However, pregnancy increases the risk of VTE as much or more than the use of COCs. The risk of VTE in women using COCs is 3 to 9 per 10,000 woman-years. The risk of VTE is highest during the first year of use of COCs and when restarting hormonal contraception after a break of 4 weeks or longer. The risk of thromboembolic disease due to COCs gradually disappears after use is discontinued.
- Use of COCs also increases the risk of arterial thromboses such as strokes and myocardial infarctions, especially in women with other risk factors for these events. COCs have been shown to increase both the relative and attributable risks of cerebrovascular events (thrombotic and hemorrhagic strokes). The risk increases with age, particularly in women over 35 years of age who smoke.
- Use COCs with caution in women with cardiovascular disease risk factors.

5.2 Liver Disease

Impaired Liver Function

Do not use levonorgestrel and ethinyl estradiol tablets and ferrous bisglycinate tablets in women with liver disease, such as acute viral hepatitis or severe (decompensated) cirrhosis of liver [see Contraindications (4)] . Acute or chronic disturbances of liver function may necessitate the discontinuation of COC use until markers of liver function return to normal and COC causation has been excluded. Discontinue levonorgestrel and ethinyl estradiol tablets and ferrous bisglycinate tablets if jaundice develops.

Liver Tumors

Levonorgestrel and ethinyl estradiol tablets and ferrous bisglycinate tablets are contraindicated in women with benign and malignant liver tumors [see Contraindications (4)] . Hepatic adenomas are associated with COC use. An estimate of the attributable risk is 3.3 cases/100,000 COC users. Rupture of hepatic adenomas may cause death through intra-abdominal hemorrhage.

Studies have shown an increased risk of developing hepatocellular carcinoma in long-term (>8 years) COC users. However, the risk of liver cancers in COC users is less than one case per million users.

5.3 Risk of Liver Enzyme Elevations with Concomitant Hepatitis C Treatment

During clinical trials with the Hepatitis C combination drug regimen that contains ombitasvir/paritaprevir/ritonavir, with or without dasabuvir, ALT elevations greater than 5 times the upper limit of normal (ULN), including some cases greater than 20 times the ULN, were significantly more frequent in women using ethinyl estradiol-containing medications, such as COCs. Discontinue levonorgestrel and ethinyl estradiol tablets and ferrous bisglycinate tablets prior to starting therapy with the combination drug regimen ombitasvir/paritaprevir/ritonavir, with or without dasabuvir [see Contraindications (4)] .

Levonorgestrel and ethinyl estradiol tablets and ferrous bisglycinate tablets can be restarted approximately 2 weeks following completion of treatment with the Hepatitis C combination drug regimen.

5.4 High Blood Pressure

Levonorgestrel and ethinyl estradiol tablets and ferrous bisglycinate tablets are contraindicated in women with uncontrolled hypertension or hypertension with vascular disease [see Contraindications (4)] . For women with well-controlled hypertension, monitor blood pressure and stop levonorgestrel and ethinyl estradiol tablets and ferrous bisglycinate tablets if blood pressure rises significantly.

An increase in blood pressure has been reported in women taking COCs, and this increase is more likely in older women with extended duration of use. The incidence of hypertension increases with increasing concentrations of progestin.

5.5 Gallbladder Disease

Studies suggest a small increased relative risk of developing gallbladder disease among COC users. Use of COCs may worsen existing gallbladder disease. A past history of COC-related cholestasis predicts an increased risk with subsequent COC use. Women with a history of pregnancy-related cholestasis may be at an increased risk for COC related cholestasis.

5.6 Carbohydrate and Lipid Metabolic Effects

Carefully monitor prediabetic and diabetic women who take levonorgestrel and ethinyl estradiol tablets and ferrous bisglycinate tablets. COCs may decrease glucose tolerance.

Consider alternative contraception for women with uncontrolled dyslipidemia. A small proportion of women will have adverse lipid changes while on COCs.

Women with hypertriglyceridemia, or a family history thereof, may be at an increased risk of pancreatitis when using COCs.

5.7 Headache

If a woman taking levonorgestrel and ethinyl estradiol tablets and ferrous bisglycinate tablets develops new headaches that are recurrent, persistent, or severe, evaluate the cause and discontinue levonorgestrel and ethinyl estradiol tablets and ferrous bisglycinate tablets if indicated.

Consider discontinuation of levonorgestrel and ethinyl estradiol tablets and ferrous bisglycinate tablets in the case of increased frequency or severity of migraine during COC use (which may be prodromal of a cerebrovascular event).

5.8 Bleeding Irregularities and Amenorrhea

Unscheduled Bleeding and Spotting

Unscheduled (breakthrough or intracyclic) bleeding and spotting sometimes occur in patients on COCs, especially during the first three months of use. If bleeding persists or occurs after previously regular cycles, check for causes such as pregnancy or malignancy. If pathology and pregnancy are excluded, bleeding irregularities may resolve over time or with a change to a different contraceptive product.

In the clinical trial with levonorgestrel 0.1 mg and ethinyl estradiol 0.02 mg tablets breakthrough bleeding and spotting was reported in 4% and 12% of cycles, respectively. Breakthrough bleeding and spotting occurred together during 11% of the cycles.

Amenorrhea and Oligomenorrhea

Women who use levonorgestrel and ethinyl estradiol tablets and ferrous bisglycinate tablets may experience amenorrhea. In the clinical trial, 2.6% of the evaluable cycles were amenorrheic. Some women may experience amenorrhea or oligomenorrhea after discontinuation of COCs, especially when such a condition was preexistent.

If scheduled (withdrawal) bleeding does not occur, consider the possibility of pregnancy. If the patient has not adhered to the prescribed dosing schedule (missed one or more active tablets or started taking them on a day later than she should have), consider the possibility of pregnancy at the time of the first missed period and take appropriate diagnostic measures. If the patient has adhered to the prescribed regimen and misses two consecutive periods, rule out pregnancy.

5.9 FD&C Yellow No. 5 Allergic-type Reaction

This product contains FD&C Yellow No. 5 (tartrazine) which may cause allergic-type reactions (including bronchial asthma) in certain susceptible persons. Although the overall incidence of FD&C Yellow No. 5 (tartrazine) sensitivity in the general population is low, it is frequently seen in patients who also have aspirin hypersensitivity.

5.10 Depression

Carefully observe women with a history of depression and discontinue levonorgestrel and ethinyl estradiol tablets and ferrous bisglycinate tablets if depression recurs to a serious degree.

5.11 Malignant Neoplasms

Breast Cancer
Levonorgestrel and ethinyl estradiol tablets and ferrous bisglycinate tablets are contraindicated in females who currently have or have had breast cancer because breast cancer may be hormonally sensitive [see Contraindications (4)].
Epidemiology studies have not found a consistent association between use of combined oral contraceptives (COCs) and breast cancer risk. Studies do not show an association between ever (current or past) use of COCs and risk of breast cancer. However, some studies report a small increase in the risk of breast cancer among current or recent users (<6 months since last use) and current users with longer duration of COC use [see Postmarketing Experience (6.2)].
Cervical Cancer
Some studies suggest that COC use has been associated with an increase in the risk of cervical cancer or intraepithelial neoplasia. However, there continues to be controversy about the extent to which such findings may be due to differences in sexual behavior and other factors.

5.12 Effect on Binding Globulins

The estrogen component of COCs may raise the serum concentrations of thyroxine-binding globulin, sex hormone-binding globulin, and cortisol-binding globulin. The dose of replacement thyroid hormone or cortisol therapy may need to be increased.

5.13 Monitoring

A woman who is taking COCs should have her blood pressure checked periodically with her healthcare provider.

5.14 Hereditary Angioedema

In women with hereditary angioedema, exogenous estrogens may induce or exacerbate symptoms of angioedema.

5.15 Chloasma

Chloasma may occasionally occur, especially in women with a history of chloasma gravidarum. Women with a tendency to chloasma should avoid exposure to the sun or ultraviolet radiation while taking levonorgestrel and ethinyl estradiol tablets and ferrous bisglycinate tablets.

6 ADVERSE REACTIONS

The following serious adverse reactions with the use of COCs are discussed elsewhere in the labeling:

- Serious cardiovascular events and stroke [see Boxed Warning and Warnings and Precautions (5.1)]
- Vascular events [see Warnings and Precautions (5.1)]
- Liver disease [see Warnings and Precautions (5.2)]

Adverse reactions commonly reported by COC users are:

- Irregular uterine bleeding
- Nausea
- Breast tenderness
- Headache

6.1 Clinical Trials Experience

Because clinical trials are conducted under widely varying conditions, adverse reaction rates observed in the clinical trials of a drug cannot be directly compared to rates in the clinical trials of another drug and may not reflect the rates observed in clinical practice.

In a clinical trial with levonorgestrel 0.1 mg and ethinyl estradiol 0.02 mg tablets, a total of 1477 healthy women of child-bearing potential were enrolled and had 7870 cycles of exposure. Of these, 792 subjects had completed 6 cycles of treatment. The women ranged in age from 17 to 49 years and 87% were Caucasian.

Common Adverse Reactions (≥ 2% of women):

- headache (14%)
- metrorrhagia (8%)
- dysmenorrhea (7%)
- nausea (7%)
- abdominal pain (4%)
- breast pain (4%)
- emotional lability (3%)
- acne (3%)
- depression (2%)
- amenorrhea (2%)
- vaginal moniliasis (2%)

At the time of the report, 133 (9%) subjects had withdrawn from the study due to adverse events. The most frequent were due to headache and metrorrhagia (1% each). Other adverse events occurring in < 1% of those who discontinued included amenorrhea, depression, emotional lability, hypertension, acne, menorrhagia, nausea, hypercholesterolemia, weight gain, dysmenorrhea, and flatulence. All other reasons for discontinuation were reported by 3 or fewer subjects.

6.2 Postmarketing Experience

Five studies that compared breast cancer risk between ever-users (current or past use) of COCs and never-users of COCs reported no association between ever use of COCs and breast cancer risk, with effect estimates ranging from 0.90 - 1.12 (Figure 1).
Three studies compared breast cancer risk between current or recent COC users (<6 months since last use) and never users of COCs (Figure 1). One of these studies reported no association between breast cancer risk and COC use. The other two studies found an increased relative risk of 1.19 - 1.33 with current or recent use. Both of these studies found an increased risk of breast cancer with current use of longer duration, with relative risks ranging from 1.03 with less than one year of COC use to approximately 1.4 with more than 8-10 years of COC use.

RR = relative risk; OR = odds ratio; HR = hazard ratio. “ever COC” are females with current or past COC use; “never COC use” are females that never used COCs.
The following additional adverse drug reactions have been reported from worldwide postmarketing experience with levonorgestrel 0.1 mg and ethinyl estradiol 0.02 mg tablets.
Because these reactions are reported voluntarily from a population of uncertain size, it is not always possible to reliably estimate their frequency or establish a causal relationship to drug exposure.
Cardiac disorder: chest pain, dyspnea, palpitations
Gastrointestinal disorders: abdominal pain, nausea, vomiting, diarrhea
General disorders and administration site conditions: chest pain, fatigue, pain, malaise, injection site pain or erythema, feeling abnormal, pyrexia, condition aggravated, asthenia
Immune system disorders: hypersensitivity reactions, including pruritus, rash, urticaria,erythema
Injury, poisoning, and procedural complications: injury
Investigations: weight decreased
Musculoskeletal and connective tissue disorders: pain in extremity, arthralgia, back pain,muscle spasm
Nervous system disorders: headache, migraine, dizziness, hypoesthesia, paresthesia
Psychiatric disorders: depression, insomnia, anxiety
Reproductive system and breast disorders: metrorrhagia, menorrhagia, hot flush, vaginal hemorrhage
Respiratory, thoracic, and mediastinal disorders: nasopharyngitis, cough
Sleep disorders and disturbances: somnolence
Vascular disorders: deep vein thrombosis, pulmonary embolism

7 DRUG INTERACTIONS

Consult the labeling of concurrently used drugs to obtain further information about interactions with hormonal contraceptives or the potential for enzyme alterations.

7.1 Effects of Other Drugs on Combined Oral Contraceptives

Substances decreasing the plasma concentrations of COCs and potentially diminishing the efficacy of COCs:

Drugs or herbal products that induce certain enzymes, including cytochrome P450 3A4 (CYP3A4), may decrease the plasma concentrations of COCs and potentially diminish the effectiveness of COCs or increase breakthrough bleeding. Some drugs or herbal products that may decrease the effectiveness of hormonal contraceptives include phenytoin, barbiturates, carbamazepine, bosentan, felbamate, griseofulvin, oxcarbazepine, rifampicin, topiramate, rifabutin, rufinamide, aprepitant, and products containing St. John’s wort. Interactions between hormonal contraceptives and other drugs may lead to breakthrough bleeding and/or contraceptive failure. Counsel women to use an alternative method of contraception or a back-up method when enzyme inducers are used with COCs, and to continue back-up contraception for 28 days after discontinuing the enzyme inducer to ensure contraceptive reliability.

Colesevelam: Colesevelam, a bile acid sequestrant, given together with a COC, has been shown to significantly decrease the AUC of ethinyl estradiol (EE). The drug interaction between the contraceptive and colesevelam was decreased when the two drug products were given 4 hours apart.

Substances increasing the plasma concentrations of COCs:

Co-administration of atorvastatin or rosuvastatin and certain COCs containing EE increase AUC values for EE by approximately 20-25%. Ascorbic acid and acetaminophen may increase plasma EE concentrations, possibly by inhibition of conjugation. CYP3A4 inhibitors, such as itraconazole, voriconazole, fluconazole, grapefruit juice, or ketoconazole may increase plasma hormone concentrations.

Human immunodeficiency virus (HIV)/ Hepatitis C virus (HCV) protease inhibitors and non-nucleoside reverse transcriptase inhibitors:

Significant changes (increase or decrease) in the plasma concentrations of estrogen and/or progestin have been noted in some cases of co-administration with HIV/HCV protease inhibitors and non-nucleoside reverse transcriptase inhibitors (decrease [e.g., nelfinavir, ritonavir, darunavir/ritonavir, (fos)amprenavir/ritonavir, lopinavir/ritonavir, tipranavir/ritonavir, boceprevir, telaprevir, nevirapine and efavirenz] or increase [e.g., indinavir, atazanavir/ritonavir and etravirine]).

7.2 Effects of Combined Oral Contraceptives on Other Drugs

Combined oral contraceptives containing EE may inhibit the metabolism of other compounds (e.g., cyclosporine, prednisolone, theophylline, tizanidine, and voriconazole) and increase their plasma concentrations. Combined oral contraceptives have been shown to decrease plasma concentrations of acetaminophen, clofibric acid, morphine, salicylic acid, temazepam and lamotrigine. Significant decrease in plasma concentration of lamotrigine has been shown, likely due to induction of lamotrigine glucuronidation. This may reduce seizure control; therefore, dosage adjustments of lamotrigine may be necessary.

Women on thyroid hormone replacement therapy may need increased doses of thyroid hormone because the serum concentration of thyroid-binding globulin increases with use of COCs [see Warnings and Precautions (5.12)] .

7.3 Concomitant Use with HCV Combination Therapy - Liver Enzyme Elevation

Do not co-administer levonorgestrel and ethinyl estradiol tablets and ferrous bisglycinate tablets with HCV drug combinations containing ombitasvir/ paritaprevir/ritonavir, with or without dasabuvir, due to potential for ALT elevations [see Warnings and Precautions (5.3)] .

7.4 Interactions with Laboratory Tests

The use of contraceptive steroids may influence the results of certain laboratory tests, such as coagulation factors, lipids, glucose tolerance, and binding proteins.

8 USE IN SPECIFIC POPULATIONS

8.1 Pregnancy

Risk Summary

Levonorgestrel and ethinyl estradiol tablets and ferrous bisglycinate tablets are contraindicated in pregnancy because there is no reason to use combined hormonal contraceptives (CHCs) in pregnancy. Discontinue levonorgestrel and ethinyl estradiol tablets and ferrous bisglycinate tablets if pregnancy occurs. Based on epidemiologic studies and meta-analyses, there is little or no increased risk of birth defects in the children of females who inadvertently use COCs during early pregnancy (See Data) .

In the U.S. general population, the estimated background risk of major birth defects and miscarriage in clinically recognized pregnancies is 2 to 4 percent and 15 to 20 percent, respectively.

Human Data

Epidemiologic studies and meta-analyses have not found an increased risk of genital or nongenital birth defects (including cardiac anomalies and limb-reduction defects) following exposure to COCs before conception or during early pregnancy.

8.2 Lactation

Risk Summary

Combined hormonal contraceptives (CHCs) and/or metabolites are present in human milk and in breast-fed infants. CHCs, including levonorgestrel and ethinyl estradiol tablets and ferrous bisglycinate tablets, can reduce milk production in breast-feeding females. This reduction can occur at any time but is less likely to occur once breast-feeding is well-established. When possible, advise the nursing female to use other methods of contraception until she discontinues breast-feeding. The developmental and health benefits of breastfeeding should be considered along with the mother’s clinical need for levonorgestrel and ethinyl estradiol tablets and ferrous bisglycinate tablets and any potential adverse effects on the breast-fed child from levonorgestrel and ethinyl estradiol tablets and ferrous bisglycinate tablets or from the underlying maternal condition.

8.4 Pediatric Use

Safety and efficacy of levonorgestrel and ethinyl estradiol tablets and ferrous bisglycinate tablets have been established in women of reproductive age. Efficacy is expected to be the same in post-pubertal adolescents under the age of 18 years as for users 18 years and older. Use of this product before menarche is not indicated.

8.5 Geriatric Use

Levonorgestrel and ethinyl estradiol tablets and ferrous bisglycinate tablets have not been studied in postmenopausal women and is not indicated in this population.

8.6 Hepatic Impairment

The pharmacokinetics of levonorgestrel and ethinyl estradiol tablets and ferrous bisglycinate tablets have not been studied in women with hepatic impairment. However, steroid hormones may be poorly metabolized in patients with hepatic impairment. Acute or chronic disturbances of liver function may necessitate the discontinuation of COC use until markers of liver function return to normal and COC causation has been excluded [see Contraindications (4) and Warnings and Precautions (5.2)] .

10 OVERDOSAGE

There have been no reports of serious ill effects from overdose of oral contraceptives, including ingestion by children. Overdosage may cause withdrawal bleeding in females and nausea.

11 DESCRIPTION

Levonorgestrel and ethinyl estradiol tablets, USP and ferrous bisglycinate tablets provide an oral contraceptive regimen consisting of 21 orange active tablets and 7 blue inactive tablets.

- 21 orange active tablets each containing 0.10 mg of levonorgestrel, d(-)-13β-ethyl-17α-ethinyl-17β-hydroxygon-4-en-3-one, a totally synthetic progestogen, and 0.02 mg of ethinyl estradiol, 17α-ethinyl-1,3,5(10)-estratriene-3, 17β-diol, an estrogenic compound.
- 7 blue inactive tablets each containing 36.5 mg ferrous bisglycinate.

The inactive ingredients present in orange active tablet are FD&C Yellow #5 Aluminum Lake, FD&C Yellow #6 Aluminum Lake, FD&C Red #40 Aluminum Lake, titanium dioxide, polyvinyl alcohol, talc, macrogol/polyethylene glycol 3350 NF, lecithin (soya), iron oxide black, lactose monohydrate, magnesium stearate and pregelatinized starch.

Each inactive blue tablet contains the following inactive ingredients: ferrous bisglycinate, citric acid, glycine, maltodextrin , silica, microcrystalline cellulose NF, magnesium stearate NF, croscarmellose sodium NF, colloidal silicon dioxide NF, hypromellose type 2910, titanium dioxide, polyethylene glycol 400, FD&C Red #40 Aluminum Lake, FD&C Yellow #6 Aluminum Lake and FD&C Blue #1 Aluminum Lake.

Levonorgestrel has the empirical formula of C 21H 28O 2and the molecular weight of 312.4, and ethinyl estradiol has the empirical formula of C 20H 24O 2and the molecular weight of 296.4.

The molecular structures are provided below:

12 CLINICAL PHARMACOLOGY

12.1 Mechanism of Action

COCs lower the risk of becoming pregnant primarily by suppressing ovulation. Other possible mechanisms may include cervical mucus changes that inhibit sperm penetration and endometrial changes that reduce the likelihood of implantation.

12.2 Pharmacodynamics

No specific pharmacodynamics studies were conducted with levonorgestrel and ethinyl estradiol tablets and ferrous bisglycinate tablets.

12.3 Pharmacokinetics

Absorption

No specific investigation of the absolute bioavailability of levonorgestrel and ethinyl estradiol tablets USP in humans has been conducted. However, literature indicates that levonorgestrel is rapidly and completely absorbed after oral administration (bioavailability about 100%) and is not subject to first-pass metabolism. Ethinyl estradiol is rapidly and almost completely absorbed from the gastrointestinal tract but, due to first-pass metabolism in gut mucosa and liver, the bioavailability of ethinyl estradiol is between 38% and 48%.

After a single dose of two levonorgestrel and ethinyl estradiol tablets to 34 women under fasting conditions, the mean (± SD) plasma area under the concentration time curve (AUC) and maximum concentration (Cmax) of levonorgestrel were 41.7 ± 18.0 ng*hour/mL and 4.4 ± 1.8ng/mL, respectively, with a median time to maximum concentration (Tmax) of 1.0 hours. The mean (±SD) plasma AUC and Cmax of ethinyl estradiol were 1167 ± 367 pg*hour/mL and 115 ± 37 pg/mL, respectively, with a median Tmax of 1.5 hours. The plasma levonorgestrel and ethinyl estradiol pharmacokinetic profi les following a single dose of two levonorgestrel and ethinyl estradiol tablets are shown in Figure 2.
Figure 2. Mean (SD) Levonorgestrel and Ethinyl Estradiol Plasma Concentrations in 34 Subjects receiving two Levonorgestrel and Ethinyl Estradiol Tablets (0.1 mg/0.02 mg) from Levonorgestrel and Ethinyl Estradiol Tablets and Ferrous Bisglycinate Tablets

Distribution

Levonorgestrel in serum is primarily bound to SHBG. Ethinyl estradiol is about 97% bound to plasma albumin. Ethinyl estradiol does not bind to SHBG, but induces SHBG synthesis.

Metabolism

Levonorgestrel:The most important metabolic pathway occurs in the reduction of the Δ4-3-oxo group and hydroxylation at positions 2α, 1β, and 16β, followed by conjugation. Most of the metabolites that circulate in the blood are sulfates of 3α, 5β-tetrahydro-levonorgestrel, while excretion occurs predominantly in the form of glucuronides. Some of the parent levonorgestrel also circulates as 17β-sulfate. Metabolic clearance rates may differ among individuals by several-fold, and this may account in part for the wide variation observed in levonorgestrel concentrations among users.

Ethinyl estradiol:Cytochrome P450 enzymes (CYP3A4) in the liver are responsible for the 2‑hydroxylation that is the major oxidative reaction. The 2-hydroxy metabolite is further transformed by methylation and glucuronidation prior to urinary and fecal excretion. Levels of Cytochrome P450 (CYP3A) vary widely among individuals and can explain the variation in rates of ethinyl estradiol 2-hydroxylation. Ethinyl estradiol is excreted in the urine and feces as glucuronide and sulfate conjugates, and undergoes enterohepatic circulation.

Excretion

The elimination half-life for levonorgestrel is approximately 34 ± 14 hours following a single dose. Levonorgestrel and its metabolites are primarily excreted in the urine (40% to 68%) and about 16% to 48% are excreted in feces. The elimination half-life of ethinyl estradiol is 17 ± 5.7 hours.

13 NONCLINICAL TOXICOLOGY

13.1 Carcinogenesis, Mutagenesis, Impairment of Fertility

[see Warnings and Precautions (5.12) and Use in Specific Populations (8.1)]

14 CLINICAL STUDIES

In a clinical trial with levonorgestrel 0.1 mg and ethinyl estradiol 0.02 mg tablets, 1,477 women aged 17-49 years, had 7,720 cycles of use. Eighty-seven percent (87%) of the women were Caucasian. The average weight was 66.4 kg with a range of 38.0-154.2 kg. Among the women in the trial, 5.3% had never used COCs.

A total of 5 pregnancies were reported. This represents an overall pregnancy rate of approximately 1 pregnancy per 100 woman-years.

16 HOW SUPPLIED/STORAGE AND HANDLING

16.1 How Supplied

Levonorgestrel and ethinyl estradiol tablets, USP and ferrous bisglycinate tablets are available in a blister pack containing 28 tablets arranged in 3 rows of 7 active tablets and 1 row of inactive tablets, as follows:

- 21 active tablets: orange, round tablet debossed with “A3” on one side; each tablet containing levonorgestrel 0.10 mg and ethinyl estradiol 0.02 mg
- 7 inactive tablets: blue, round tablet debossed with “F1” on one side; each tablet containing ferrous bisglycinate 36.5 mg

Levonorgestrel and ethinyl estradiol tablets, USP and ferrous bisglycinate tablets are available in the following conﬁgurations:

Carton of one 1-cycle blister pack (NDC 42192-623-28)

Carton of three 1-cycle blister packs (NDC 42192-623-03)

16.2 Storage Conditions

- Store at 20° to 25°C (68° to 77°F); excursions permitted to 15° to 30°C (59° to 86°F). [See USP controlled room temperature].
- Protect from light

Keep out of the reach of children.

17 PATIENT COUNSELING INFORMATION

See FDA-approved patient labeling(Patient Information and Instructions for Use).

Counsel patients on the following information:

- Cigarette smoking increases the risk of serious cardiovascular events from COC use, and that women who are over 35 years old and smoke should not use COCs [see Boxed Warning] .
- Increased risk of VTE compared to non-users of COCs is greatest after initially starting a COC or restarting (following a 4-week or greater pill-free interval) the same or a different COC [see Warnings and Precautions (5.1)] .
- Levonorgestrel and ethinyl estradiol tablets and ferrous bisglycinate tablets do not protect against HIV-infection (AIDS) and other sexually transmitted diseases.
- Levonorgestrel and ethinyl estradiol tablets and ferrous bisglycinate tablets are not to be used during pregnancy; if pregnancy occurs during use of levonorgestrel and ethinyl estradiol tablets and ferrous bisglycinate tablets, instruct the patient to stop further use [see Use in Specific Populations (8.1)] .
- Take one tablet daily by mouth at the same time every day. Instruct patients what to do in the event pills are missed [see Dosage and Administration (2.3)] .
- Use a back-up or alternative method of contraception when enzyme inducers are used with levonorgestrel and ethinyl estradiol tablets and ferrous bisglycinate tablets [see Drug Interactions (7.1)] .
- COCs may reduce breast milk production; this is less likely to occur if breastfeeding is well established [see Use in Specific Populations (8.2)] .
- A woman who starts COCs postpartum and who has not yet had a period should use an additional method of contraception until she has taken a white tablet for 7 consecutive days [see Dosage and Administration (2.2)] .
- Amenorrhea may occur. Consider pregnancy in the event of amenorrhea at the time of the first missed period. Rule out pregnancy in the event of amenorrhea in two or more consecutive cycles [see Warnings and Precautions (5.8)] .

Manufactured for:

Acella Pharmaceuticals, LLC.,
1880 McFarland Pkwy.,
Alpharetta, GA 30005
1-800-541-4802

Manufactured by:

Novast Laboratories, Ltd.,
Nantong, China 226009.

Date: 08/2022

I0162 Rev. B

PATIENT INFORMATION

Levonorgestrel and Ethinyl Estradiol (LEE-voe-nor-JES-trel and EH-thih-nill-ess-tra-DYE-ole) Tablets, USP and Ferrous Bisglycinate (FARR-ouss BISS-glyy-sinn-ATE) Tablets
for oral administration

What is the most important information I should know about levonorgestrel and ethinyl estradiol tablets and ferrous bisglycinate tablets?

Do not use levonorgestrel and ethinyl estradiol tablets and ferrous bisglycinate tablets if you smoke cigarettes and are over 35 years old. Smoking increases your risk of serious cardiovascular side effects (heart and blood vessel problems) from birth control pills, including death from heart attack, blood clots or stroke. This risk increases with age and the number of cigarettes you smoke.

What are levonorgestrel and ethinyl estradiol tablets and ferrous bisglycinate tablets?

Levonorgestrel and ethinyl estradiol tablets and ferrous bisglycinate tablets are birth control pills (oral contraceptive) used by women to prevent pregnancy.

Levonorgestrel and ethinyl estradiol tablets and ferrous bisglycinate tablets do not protect against HIV infections (AIDS) and other sexually transmitted infections.

How do levonorgestrel and ethinyl estradiol tablets and ferrous bisglycinate tablets work for contraception?

Your chance of getting pregnant depends on how well you follow the directions for taking your birth control pills. The better you follow the directions, the less chance you have of getting pregnant.

Based on the results of one clinical study of a 28-day regimen of levonorgestrel 0.1 mg/ethinyl estradiol 0.02 mg tablets, about 1 out of 100 women may get pregnant within the first year they use levonorgestrel and ethinyl estradiol tablets and ferrous bisglycinate tablets.

The following chart shows the chance of getting pregnant for women who use different methods of birth control. Each box on the chart contains a list of birth control methods that are similar in effectiveness. The most effective methods are at the top of the chart. The box on the bottom of the chart shows the chance of getting pregnant for women who do not use birth control and are trying to get pregnant.

Do not take levonorgestrel and ethinyl estradiol tablets and ferrous bisglycinate tablets if you:

- smoke and are over 35 years of age
- have or have had blood clots in your arms, legs, lungs, or eyes
- have a problem with your blood that makes it clot more than normal
- have certain heart valve problems or irregular heart beat that increases your risk of having blood clots
- had a stroke
- had a heart attack
- have high blood pressure that cannot be controlled by medicine
- have diabetes with kidney, eye, nerve, or blood vessel damage
- have certain kinds of severe migraine headaches with aura, numbness, weakness or changes in vision, or any migraine headaches if you are over 35 years of age
- have liver problems, including liver tumors
- have any unexplained vaginal bleeding
- are pregnant
- have or have had breast cancer or any cancer that is sensitive to female hormones
- are allergic to levonorgestrel, ethinyl estradiol, ferrous bisglycinate or any of the ingredients in levonorgestrel and ethinyl estradiol tablets and ferrous bisglycinate tablets. Some people who are allergic to aspirin may also be allergic to FD&C Yellow No. 5 (tartrazine). FD&C Yellow No. 5 (tartrazine) is an ingredient in levonorgestrel and ethinyl estradiol tablets and ferrous bisglycinate tablets which also may cause an allergic type reaction such as bronchial asthma. See the end of this Patient Information leaflet for a complete list of ingredients in levonorgestrel and ethinyl estradiol tablets and ferrous bisglycinate tablets.
- take any Hepatitis C drug combination containing ombitasvir/paritaprevir/ritonavir, with or without dasabuvir. This may increase levels of the liver enzyme “alanine aminotransferase” (ALT) in the blood.

If any of these conditions happen while you are taking levonorgestrel and ethinyl estradiol tablets and ferrous bisglycinate tablets, stop taking levonorgestrel and ethinyl estradiol tablets and ferrous bisglycinate tablets right away and talk to your healthcare provider. Use non-hormonal contraception when you stop taking levonorgestrel and ethinyl estradiol tablets and ferrous bisglycinate tablets.

Before you take levonorgestrel and ethinyl estradiol tablets and ferrous bisglycinate tablets, tell your health care provider about all of your medical conditions, including if you:

- are scheduled for surgery. Levonorgestrel and ethinyl estradiol tablets and ferrous bisglycinate tablets may increase your risk of blood clots after surgery. You should stop using your levonorgestrel and ethinyl estradiol tablets and ferrous bisglycinate tablets at least 4 weeks before you have surgery and not restart it until at least 2 weeks after your surgery.
- are pregnant or think you may be pregnant
- are depressed now or have been depressed in the past
- had yellowing of your skin or eyes (jaundice) caused by pregnancy (cholestasis of pregnancy)
- are breastfeeding or plan to breastfeed. Levonorgestrel and ethinyl estradiol tablets and ferrous bisglycinate tablets may decrease the amount of breast milk you make. A small amount of the hormones in levonorgestrel and ethinyl estradiol tablets and ferrous bisglycinate tablets may pass into your breast milk. Talk to your healthcare provider about the best birth control method for you while breastfeeding.

Tell your healthcare provider about all the medicines you take,including prescription and over-the-counter medicines, vitamins and herbal supplements.

Levonorgestrel and ethinyl estradiol tablets and ferrous bisglycinate tablets may affect the way other medicines work, and other medicines may affect how well levonorgestrel and ethinyl estradiol tablets and ferrous bisglycinate tablets work.

Know the medicines you take. Keep a list of them to show your healthcare provider and pharmacist when you get a new medicine.

How should I take levonorgestrel and ethinyl estradiol tablets and ferrous bisglycinate tablets?

- Read the detailed Instructions for Use at the end of this Patient Information leaflet about the right way to take your levonorgestrel and ethinyl estradiol tablets and ferrous bisglycinate tablets.

What are the possible serious side effects of levonorgestrel and ethinyl estradiol tablets and ferrous bisglycinate tablets?

- Like pregnancy, levonorgestrel and ethinyl estradiol tablets and ferrous bisglycinate tablets may cause serious side effects, including blood clots in your lungs, heart attack, or a stroke that may lead to death. Some other examples of serious blood clots include blood clots in the legs or eyes.
  Serious blood clots can happen especially if you smoke, are obese, or are older than 35 years of age. Serious blood clots are more likely to happen when you:
  - first start taking birth control pills
  - restart the same or different birth control pills after not using them for a month or more

Call your healthcare provider or go to a hospital emergency room right away if you have:

-
  - leg pain that will not go away
  - sudden severe shortness of breath
  - sudden change in vision or blindness
  - chest pain
  - a sudden, severe headache unlike your usual headaches
  - weakness or numbness in your arm or leg
  - trouble speaking

Other serious side effects include:

- liver problems, including:
  - rare liver tumors
  - jaundice (cholestasis), especially if you previously had cholestasis of pregnancy. Call your healthcare provider if you have yellowing of your skin or eyes.
- high blood pressure.You should see your health care provider to check your blood pressure regularly.
- gallbladder problems
- changes in the sugar and fat (cholesterol and triglycerides) levels in your blood
- new or worsening headaches including migraine headaches
- depression
- possible cancer in your breast and cervix
- swelling of your skin especially around your mouth, eyes, and in your throat (angioedema).Call your healthcare provider if you have a swollen face, lips, mouth tongue or throat, which may lead to difficulty swallowing or breathing. Your chance of having angioedema is higher if you have a history of angioedema.
- dark patches of skin around your forehead, nose, cheeks and around your mouth, especially during pregnancy (chloasma).Women who tend to get chloasma should avoid spending a long time in sunlight, tanning booths, and under sun lamps while taking levonorgestrel and ethinyl estradiol tablets and ferrous bisglycinate tablets. Use sunscreen if you have to be in the sunlight.

What are the most common side effects of levonorgestrel and ethinyl estradiol tablets and ferrous bisglycinate tablets?

The most common side effects of levonorgestrel and ethinyl estradiol tablets and ferrous bisglycinate tablets include:

- headache (including migraine)
- irregular vaginal bleeding (including absence of period)
- nausea
- breast tenderness, pain and discomfort
- stomach (abdominal) pain
- pain with your periods (menstrual cycle)
- mood changes, including depression
- acne
- vaginal infections

These are not all the possible side effects of levonorgestrel and ethinyl estradiol tablets and ferrous bisglycinate tablets. Call your doctor for medical advice about side effects. You may report side effects to the FDA at 1-800-FDA-1088.

What else should I know about taking levonorgestrel and ethinyl estradiol tablets and ferrous bisglycinate tablets?

- If you are scheduled for any lab tests, tell your healthcare provider you are taking levonorgestrel and ethinyl estradiol tablets and ferrous bisglycinate tablets. Certain blood tests may be affected by levonorgestrel and ethinyl estradiol tablets and ferrous bisglycinate tablets.

How should I store levonorgestrel and ethinyl estradiol tablets and ferrous bisglycinate tablets?

- Store levonorgestrel and ethinyl estradiol tablets and ferrous bisglycinate tablets at room temperature between 68°F to 77°F (20°C to 25°C).
- Keep levonorgestrel and ethinyl estradiol tablets and ferrous bisglycinate tablets and all medicines out of the reach of children.
- Store away from light.

General information about the safe and effective use of levonorgestrel and ethinyl estradiol tablets and ferrous bisglycinate tablets.

Medicines are sometimes prescribed for purposes other than those listed in a Patient Information leaflet. Do not use levonorgestrel and ethinyl estradiol tablets and ferrous bisglycinate tablets for a condition for which it was not prescribed. Do not give levonorgestrel and ethinyl estradiol tablets and ferrous bisglycinate tablets to other people, even if they have the same symptoms that you have. It may harm them. You can ask your pharmacist or healthcare provider for information about levonorgestrel and ethinyl estradiol tablets and ferrous bisglycinate tablets that is written for health professionals.

Do birth control pills cause cancer?

It is not known if hormonal birth control pills cause breast cancer. Some studies, but not all, suggest that there could be a slight increase in the risk of breast cancer among current users with longer duration of use.
If you have breast cancer now, or have had it in the past, do not use hormonal birth control because some breast cancers are sensitive to hormones.
Women who use birth control pills may have a slightly higher chance of getting cervical cancer. However, this may be due to other reasons such as having more sexual partners.

What if I want to become pregnant?

You may stop taking the pill whenever you wish. Consider a visit with your healthcare provider for a pre-pregnancy checkup before you stop taking the pill.

What should I know about my period when taking levonorgestrel and ethinyl estradiol tablets and ferrous bisglycinate tablets?

Some women may miss a period. Irregular vaginal bleeding or spotting may happen while you are taking levonorgestrel and ethinyl estradiol tablets and ferrous bisglycinate tablets, especially during the first few months of use. This usually is not a serious problem. If the irregular vaginal bleeding or spotting continues or happens again after you have had regular menstrual cycles call your healthcare provider. It is important to continue taking your pills on a regular schedule to prevent a pregnancy.

What if I miss my scheduled period when using levonorgestrel and ethinyl estradiol tablets and ferrous bisglycinate tablets?

Some women miss periods on hormonal birth control, even when they are not pregnant. However, if you go 2 or more months in a row without a period, or you miss your period after a month where you did not use all of your levonorgestrel and ethinyl estradiol tablets and ferrous bisglycinate tablets correctly, call your healthcare provider because you may be pregnant. Also call your healthcare provider if you have symptoms of pregnancy such as morning sickness or unusual breast tenderness. Stop taking levonorgestrel and ethinyl estradiol tablets and ferrous bisglycinate tablets if you are pregnant.

What are the ingredients in levonorgestrel and ethinyl estradiol tablets and ferrous bisglycinate tablets?

Active ingredients:Orange tablets: levonorgestrel and ethinyl estradiol.

Inactive ingredients: Orange tablets: FD&C Yellow #5 Aluminum Lake, FD&C Yellow #6 Aluminum Lake, FD&C Red #40 Aluminum Lake, titanium dioxide, polyvinyl alcohol, talc, macrogol/polyethylene glycol 3350 NF, lecithin (soya), iron oxide black, lactose monohydrate, magnesium stearate and pregelatinized starch.

Inactive ingredients:Blue tablets: ferrous bisglycinate, citric acid NF, glycine, maltodextrin NF, silica, microcrystalline cellulose NF, magnesium stearate NF, croscarmellose sodium NF, colloidal silicon dioxide NF, hypromellose type 2910, titanium dioxide, polyethylene glycol 400, FD&C Red #40 Aluminum Lake, FD&C Yellow #6 Aluminum Lake and FD&C Blue #1 Aluminum Lake.

For more information, go to www.acellapharma.com or call 1-800-541-4802.

INSTRUCTIONS FOR USE

Levonorgestrel and Ethinyl Estradiol (LEE-voe-nor-JES-trel and EH-thih-nill-ess-tra-DYE-ole) Tablets, USP and Ferrous Bisglycinate (FARR-ouss BISS-glyy-sinn-ATE) Tablets
for oral administration

Important Information about taking levonorgestrel and ethinyl estradiol tablets and ferrous bisglycinate tablets

- Take 1 pill every day at the same time. Take the pills in the order directed on your blister pack.
  Both the orange pills and the blue pills should be swallowed whole.
- Do not skip your pills, even if you do not have sex often. If you miss pills (including starting the pack late) you could get pregnant. The more pills you miss, the more likely you are to get pregnant.
- If you have trouble remembering to take levonorgestrel and ethinyl estradiol tablets and ferrous bisglycinate tablets, talk to your healthcare provider. When you first start taking levonorgestrel and ethinyl estradiol tablets and ferrous bisglycinate tablets, spotting or light bleeding in between your periods may occur. Contact your healthcare provider if this does not go away after a few months.
- You may feel sick to your stomach (nauseous), especially during the first few months of taking levonorgestrel and ethinyl estradiol tablets and ferrous bisglycinate tablets. If you feel sick to your stomach, do not stop taking the pill. The problem will usually go away. If your nausea does not go away, call your healthcare provider.
- Missing pills can also cause spotting or light bleeding, even when you take the missed pills later. On the days you take 2 pills to make up for missed pills (see below), you could also feel a little sick to your stomach.
- Some women miss periods on hormonal birth control, even when they are not pregnant. However, if you miss a period and have not taken levonorgestrel and ethinyl estradiol tablets and ferrous bisglycinate tablets according to directions, or miss 2 periods in a row, or feel like you may be pregnant, call your health care provider. If you have a positive pregnancy test, you should stop taking levonorgestrel and ethinyl estradiol tablets and ferrous bisglycinate tablets.
- If you have vomiting or diarrhea within 3 to 4 hours of taking your pill, take another pill of the same color from your extra blister pack. If you do not have an extra blister pack, take the next pill in your blister pack.
- Continue taking all your remaining pills in order. Start the first pill of your next blister pack the day after finishing your current blister pack. This will be 1 day earlier than originally scheduled. Continue on your new schedule.
- If you have vomiting or diarrhea for more than 1 day, your birth control pills may not work as well. Use an additional birth control method, like condoms or a spermicide, until you check with your healthcare provider.
- Stop taking levonorgestrel and ethinyl estradiol tablets and ferrous bisglycinate tablets at least 4 weeks before you have major surgery and do not restart it until at least 2 weeks after your surgery. Be sure to use other forms of contraception (like condoms or spermicide) during this time period.

Before you start taking levonorgestrel and ethinyl estradiol tablets and ferrous bisglycinate tablets

- Decide what time of day you want to take your pill. It is important to take it at the same time every day and in the order as directed on your blister pack.
- Have backup contraception (condoms or spermicide) available and an extra full pack of pills as needed.

When should I start taking levonorgestrel and ethinyl estradiol tablets and ferrous bisglycinate tablets?

If you start taking levonorgestrel and ethinyl estradiol tablets and ferrous bisglycinate tablets and you have not used a hormonal birth control method before:

- There are 2 ways to start taking your birth control pills.
  - You can either start on a Sunday (Sunday Start) or
  - You can start on the first day (Day 1) of your natural menstrual period (Day 1 Start).

Your healthcare provider should tell you when to start taking your birth control pill.

If you use the Sunday Start, use non-hormonal back-up contraception such as condoms or spermicide for the first 7 days that you take levonorgestrel and ethinyl estradiol tablets and ferrous bisglycinate tablets. You do not need back-up contraception if you use the Day 1 Start.

If you start taking levonorgestrel and ethinyl estradiol tablets and ferrous bisglycinate tablets and you are switching from another birth control pill:

- Start your new levonorgestrel and ethinyl estradiol tablets and ferrous bisglycinate tablets pack on the same day that you would start the next pack of your previous birth control method.
- Do not continue taking the pills from your previous birth control pack.

If you start taking levonorgestrel and ethinyl estradiol tablets and ferrous bisglycinate tablets and previously used a vaginal ring or transdermal patch:

- Start using levonorgestrel and ethinyl estradiol tablets and ferrous bisglycinate tablets on the day you would have reapplied the next ring or patch.

If you start taking levonorgestrel and ethinyl estradiol tablets and ferrous bisglycinate tablets and you are switching from a progestin-only method such as an implant or injection:

- Start taking levonorgestrel and ethinyl estradiol tablets and ferrous bisglycinate tablets on the day of removal of your implant or on the day when you would have had your next injection.

If you start taking levonorgestrel and ethinyl estradiol tablets and ferrous bisglycinate tablets and you are switching from an intrauterine device or system (IUD or IUS):

- Start taking levonorgestrel and ethinyl estradiol tablets and ferrous bisglycinate tablets on the day of removal of your IUD or IUS.
- You do not need back-up contraception if your IUD or IUS is removed on the first day (Day 1) of your period. If your IUD or IUS is removed on any other day, use non-hormonal back-up contraception such as condoms or spermicide for the first 7 days that you take levonorgestrel and ethinyl estradiol tablets and ferrous bisglycinate tablets.

Keep a calendar to track your period:

If this is the first time you are taking birth control pills, read, “ When should I start taking levonorgestrel and ethinyl estradiol tablets and ferrous bisglycinate tablets?” above. Follow these instructions for either a Sunday Start or a Day 1 Start.

Sunday Start:

You will use a Sunday Start if your healthcare provider told you to take your first pill on a Sunday. Use non-hormonal back-up contraception such as condoms or spermicide for the first 7 days of the first cycle that you take levonorgestrel and ethinyl estradiol tablets and ferrous bisglycinate tablets.

Instructions for using your pill pack

- Look at your levonorgestrel and ethinyl estradiol tablets and ferrous bisglycinate tablets pill pack. See Figure A.
- Take pill 1 on the Sunday after your period starts.
- If your period starts on a Sunday, take pill “ 1” that day and refer to Day 1 Start instructions below.
- Take 1 pill every day in the order on the blister pack at the same time each day for 28 days.
- After taking the last pill on Day 28 from the blister pack, start taking the first pill from a new pack, on the same day of the week as the first pack (Sunday). Take the first pill in the new pack whether or not you are having your period.

Day 1 Start:

You will use a Day 1 Start if your healthcare provider told you to take your first pill (Day 1) on the first day of your period.

- Take 1 pill every day in the order of the blister pack, at the same time each day, for 28 days.
- After taking the last pill on Day 28 from the pill dispenser, start taking the first pill from a new pack, on the same day of the week as the first pack. Take the first pill in the new pack whether or not you are having your period.

Instructions for using your pill pack:

Step 1.

Look at your levonorgestrel and ethinyl estradiol tablets and ferrous bisglycinate tablets pill pack. See Figure A.

The levonorgestrel and ethinyl estradiol and ferrous bisglycinate pill pack has:

- 21 orange (active) pills with hormone for Week 1 through Week 3.
- 7 blue (inactive) pills without hormones for Week 4

Step 2.

Find what day of the week you are to start taking pills. If your period begins on a day other than Sunday, place the day label strip that starts with the first day of your period. For example, if your period begins on Monday, place the day label strip with Monday as the first day. See Figure B.

Step 3.

Remove the orange pill by pressing the pill through the foil in the bottom of the pill pack. Continue taking the orange pills for 21 days.

Step 4.

On the first day of Week 4 start taking the blue pills. Take the blue pill for 7 days. Your period should start during this time.

Step 5.

When you have taken all of the blue pills in your pill pack, get a new pill pack and start taking the orange pills.

- For a Day 1 start: Begin your next pill pack on the same day of the week as your first cycle pill pack.
- For a Sunday Start: Begin your next pill pack on Sunday.

What should I do if I miss any levonorgestrel and ethinyl estradiol and ferrous bisglycinate pills?

If you miss 1 pill in Weeks 1, 2, or 3, follow these steps:

- Take it as soon as you remember. Take the next pill at your regular time. This means you may take 2 pills in 1 day.
- Then continue taking 1 pill every day until you finish the pack.
- You do not need to use a back-up birth control method if you have sex.

If you miss 2 pills in Week 1 or Week 2 of your pack, follow these steps:

- Take the 2 missed pills as soon as possible and the next 2 pills the next day.
- Then continue to take 1 pill every day until you finish the pack.
- Use a non-hormonal birth control method (such as a condom or spermicide) as a back-up if you have sex during the first 7 days after missing your pills.

If you miss 2 pills in a row in Week 3, or you miss 3 or more pills in a row during Weeks 1, 2, or 3 of the pack, follow these steps:

- If you are a Day 1 Starter:
  - Throw out the rest of the pill pack and start a new pack that same day.
- If you are a Sunday Starter:
  - Keep taking 1 pill every day until Sunday. On Sunday, throw out the rest of the pack and start a new pack of pills that same day.
- You may not have your period this month but this is expected. However, if you miss your period 2 months in a row, call your healthcare provider because you might be pregnant.
- You could become pregnant if you have sex during the first 7 days after you restart your pills. You should use a non-hormonal birth control method (such as a condom or spermicide) as a back-up if you have sex during the first 7 days after you restart your pills.

If you have any questions or are unsure about the information in this leaflet, call your healthcare provider. They have a more technical leaflet called the Professional Labeling which you may wish to read.

This Patient Information and Instructions for Use has been approved by the U.S. Food and Drug Administration.

Manufactured for:

Acella Pharmaceuticals, LLC.,
1880 McFarland Pkwy.,
Alpharetta, GA 30005
1-800-541-4802

Manufactured by:

Novast Laboratories, Ltd.,
Nantong, China 226009.

Date: 08/2022 L-0322 Rev 0822-02

Rev. B

PRINCIPAL DISPLAY PANEL - CARTON FRONT

NDC 42192-623-28
28-day regimen

1 Blister Pack
28 tablets

28-day regimen
1 Blister Pack,28 tablets
Rx Only

levonorgestrel and ethinyl estradiol tablets, USP, and ferrous bisglycinate tablets 0.1mg/0.02mg and 36.5mg

This product is intended to prevent pregnancy. It does not protect against HIV infection (AIDS) and other sexually transmitted diseases.

The inactive ingredients present in orange active tablet are FD&C Yellow #5 Aluminum Lake, FD&C Yellow #6 Aluminum Lake, FD&C Red #40 Aluminum Lake, titanium dioxide, polyvinyl alcohol, talc, macrogol/polyethylene glycol 3350 NF, lecithin (soya), iron oxide black, lactose monohydrate, magnesium stearate and pregelatinized starch.

Each inactive blue tablet contains the following inactive ingredients: ferrous bisglycinate, citric acid, glycine, maltodextrin , silica, microcrystalline cellulose NF, magnesium stearate NF, croscarmellose sodium NF, colloidal silicon dioxide NF, hypromellose type 2910, titanium dioxide, polyethylene glycol 400, FD&C Red #40 Aluminum Lake, FD&C Yellow #6 Aluminum Lake and FD&C Blue #1 Aluminum Lake.

1 Blister Pack, 28 tablets

Levonorgestrel and ethinyl estradiol tablets and ferrous bisglycinate tablets

WARNING:CIGARETTE SMOKING AND SERIOUS CARDIOVASCULAR EVENTS.
Cigarette smoking increases the risk of serious cardiovascular events from combination oral contraceptive (COC) use. This risk increases with age, particularly in women over 35 years of age, and with the number of cigarettes smoked. For this reason, COCs are contraindicated in women who are over 35 years of age and smoke.

NDC 42192-623-28
28-day regimen

PRINCIPAL DISPLAY PANEL - CARTON BACK

1 Blister Pack,
28 tablets

28-day regimen
1 blister pack,28 tablets
Rx Only

Levonorgestrel and ethinyl estradiol tablets, USP and ferrous bisglycinate tablets 0.1mg/0.02mg and 36.5mg

IMPORTANT - Note to Dispensing Pharmacist:Each compact dispenser contains a combination Patient Information and Instructions For Use Insert with Day Label Stickers. This should be included with each package dispensed to the patient.

Each active orange tablet (21) contains levonorgestrel 0.1 mg and ethinyl estradiol 0.02 mg.
Each inactive blue tablet (7) contains ferrous bisglycinate 36.5 mg.

Contains color additives including FD&C Yellow No. 5 (tartrazine).

Usual Dosage:One orange tablet daily for 21 consecutive days followed by one blue placebo tablet for 7 consecutive days according to prescribed schedule.

See enclosed prescribing information.

Store at 20° to 25°C (68° to 77°F); Excursions permitted to 15° to 30°C (59° to 86°F). [See USP controlled room temperature.]
Protect from light.

Keep out of the reach of children.

WARNING:Accidental overdose of iron-containing products is a leading cause of fatal poisoning in children under 6. Keep this product out of reach of children. In case of accidental overdose, call a doctor or poison control center immediately.

Manufactured for:
Avion Pharmaceuticals, LLC., Alpharetta, GA 30005
1-800-541-4802

Manufactured by:
Novast Laboratories, Ltd., Nantong, China 226009

Rx Only

L-0319 Rev 0721-01 Iss. 07/2021 Rev A C0248